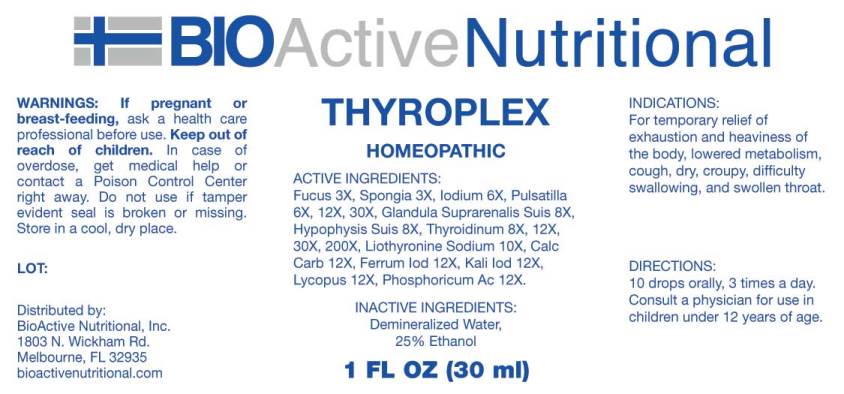 DRUG LABEL: Thyroplex
NDC: 43857-0614 | Form: LIQUID
Manufacturer: BioActive Nutritional
Category: homeopathic | Type: HUMAN OTC DRUG LABEL
Date: 20231013

ACTIVE INGREDIENTS: FUCUS VESICULOSUS 3 [hp_X]/1 mL; SPONGIA OFFICINALIS SKELETON, ROASTED 3 [hp_X]/1 mL; IODINE 6 [hp_X]/1 mL; PULSATILLA VULGARIS WHOLE 6 [hp_X]/1 mL; SUS SCROFA ADRENAL GLAND 8 [hp_X]/1 mL; SUS SCROFA PITUITARY GLAND 8 [hp_X]/1 mL; THYROID 8 [hp_X]/1 mL; LEVOTHYROXINE 10 [hp_X]/1 mL; OYSTER SHELL CALCIUM CARBONATE, CRUDE 12 [hp_X]/1 mL; FERROUS IODIDE 12 [hp_X]/1 mL; POTASSIUM IODIDE 12 [hp_X]/1 mL; LYCOPUS VIRGINICUS WHOLE 12 [hp_X]/1 mL; PHOSPHORIC ACID 12 [hp_X]/1 mL
INACTIVE INGREDIENTS: WATER; ALCOHOL

DRUG FACTS:

ACTIVE INGREDIENTS:

Fucus Vesiculosus 3X, Spongia Tosta 3X, Iodium 6X, Pulsatilla 6X, 12X, 30X, Glandula Suprarenalis Suis 8X, Hypophysis Suis 8X, Thyroidinum 8X, 12X, 30X, 200X, Levothyroxinum 10X, Calcarea Carbonica 12X, Ferrum Iodatum 12X, Kali Iodatum 12X, Lycopus Virginicus 12X, Phosphoricum Acidum 12X.

INDICATIONS:

For temporary relief of exhaustion and heaviness of the body, lowered metabolism, cough, dry, croupy, difficulty swallowing, and swollen throat.

WARNINGS:

If pregnant or breast-feeding, ask a health care professional before use.

Keep out of reach of children. In case of overdose, get medical help or contact a Poison Control Center right away.

Do not use if tamper evident seal is broken or missing.

Store in cool, dry place.

KEEP OUT OF REACH OF CHILDREN:

In case of overdose, get medical help or contact a Poison Control Center right away.

DIRECTIONS:

10 drops orally, 3 times a day. Consult a physician for use in children under 12 years of age.

INDICATIONS:

For temporary relief of exhaustion and heaviness of the body, lowered metabolism, cough, dry, croupy, difficulty swallowing, and swollen throat.

INACTIVE INGREDIENTS:

Demineralized Water, 25% Ethanol

QUESTIONS:

Distributed by:

BioActive Nutritional, Inc.

1803 N. Wickham Rd.

Melbourne, FL 32935

bioactivenutritional.com

PACKAGE LABEL DISPLAY:

BIOActive Nutritional

THYROPLEX

HOMEOPATHIC

1 FL OZ (30 ml)